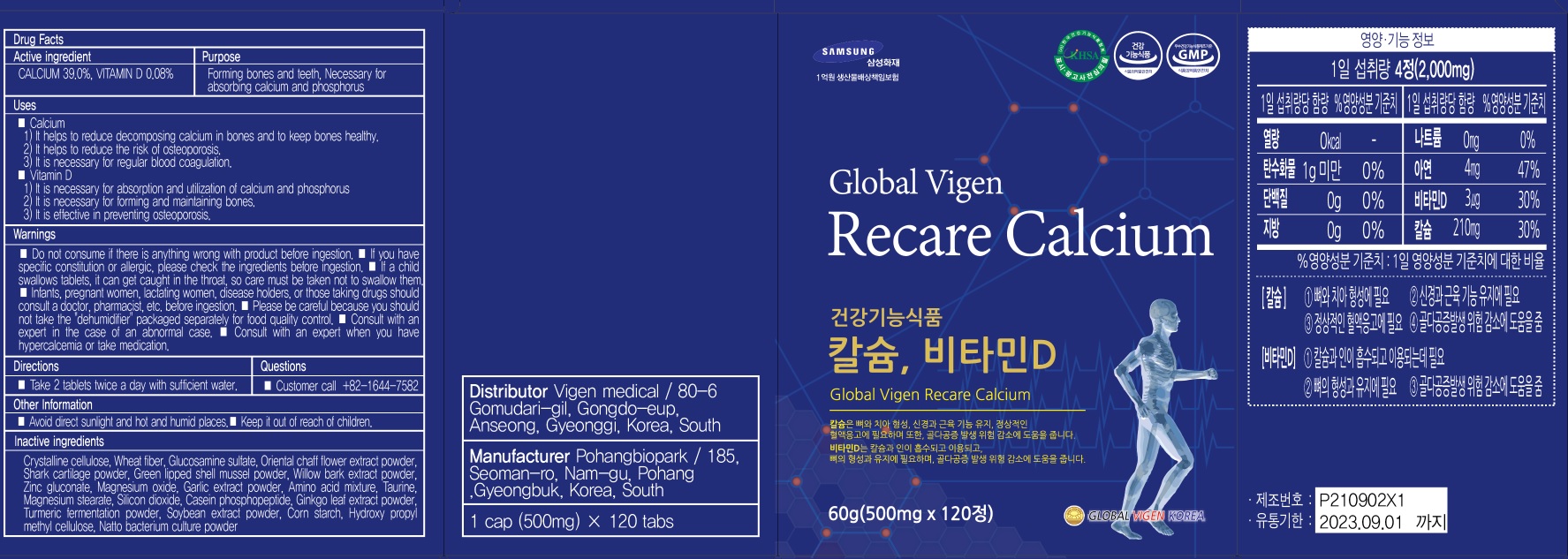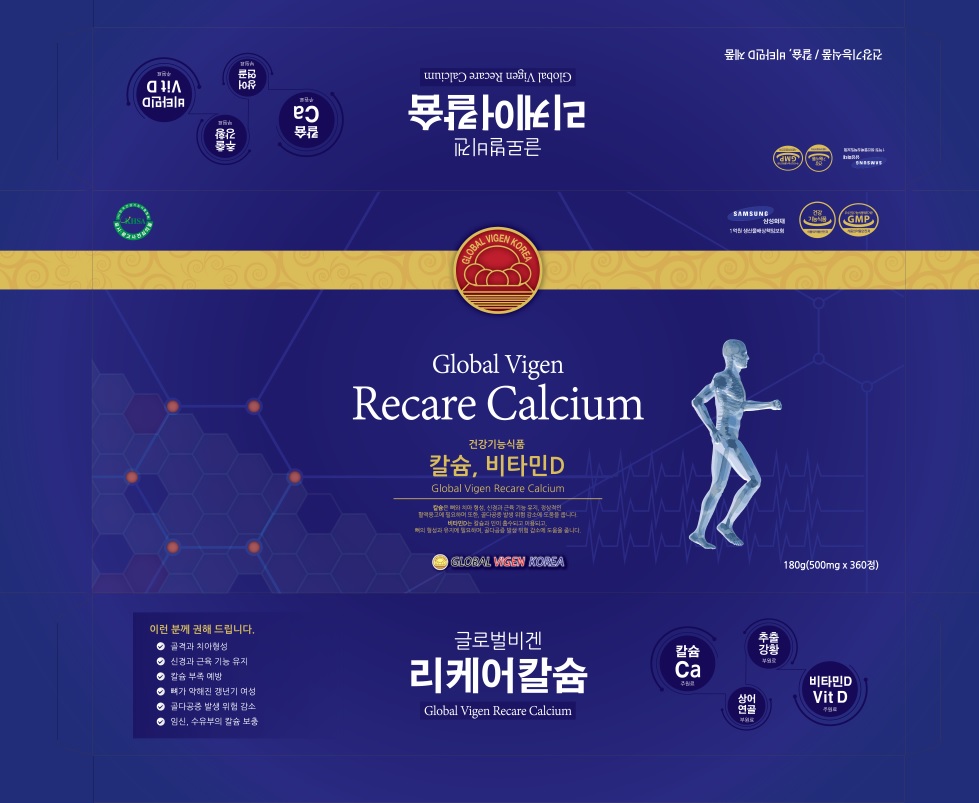 DRUG LABEL: Global Vigen Recare Calcium
NDC: 82437-010 | Form: TABLET
Manufacturer: Vigen medical
Category: otc | Type: HUMAN OTC DRUG LABEL
Date: 20211215

ACTIVE INGREDIENTS: CALCIUM 195 mg/500 mg; VITAMIN D 0.4 mg/500 mg
INACTIVE INGREDIENTS: MICROCRYSTALLINE CELLULOSE; GLUCOSAMINE SULFATE

ACTIVE INGREDIENT

CALCIUM 39.0%
VITAMIN D 0.08%

INACTIVE INGREDIENTS

Crystalline cellulose, Wheat fiber, Glucosamine sulfate, Oriental chaff flower extract powder, Shark cartilage powder, Green lipped shell mussel powder, Willow bark extract powder, Zinc gluconate, Magnesium oxide, Garlic extract powder, Amino acid mixture, Taurine, Magnesium stearate, Silicon dioxide, Casein phosphopeptide, Ginkgo leaf extract powder, Turmeric fermentation powder, Soybean extract powder, Corn starch, Hydroxy propyl methyl cellulose, Natto bacterium culture powder

PURPOSE

Forming bones and teeth
Necessary for absorbing calcium and phosphorus

WARNINGS

■ Do not consume if there is anything wrong with product before ingestion.
■ If you have specific constitution or allergic, please check the ingredients before ingestion.
■ If a child swallows tablets, it can get caught in the throat, so care must be taken not to swallow them.
■ Infants, pregnant women, lactating women, disease holders, or those taking drugs should consult a doctor, pharmacist, etc. before ingestion.
■ Please be careful because you should not take the "dehumidifier" packaged separately for food quality control.
■ Consult with an expert in the case of an abnormal case.
■ Consult with an expert when you have hypercalcemia or take medication.

KEEP OUT OF REACH OF CHILDREN

Uses

■ Calcium
1) It helps to reduce decomposing calcium in bones and to keep bones healthy.
2) It helps to reduce the risk of osteoporosis.
3) It is necessary for regular blood coagulation.
■ Vitamin D
1) It is necessary for absorption and utilization of calcium and phosphorus
2) It is necessary for forming and maintaining bones.
3) It is effective in preventing osteoporosis.

Directions

■ Take 2 tablets twice a day with sufficient water.

Other Information

■ Avoid direct sunlight and hot and humid places.
■ Keep it out of reach of children.

Questions

■ Customer call
+82-1644-7582